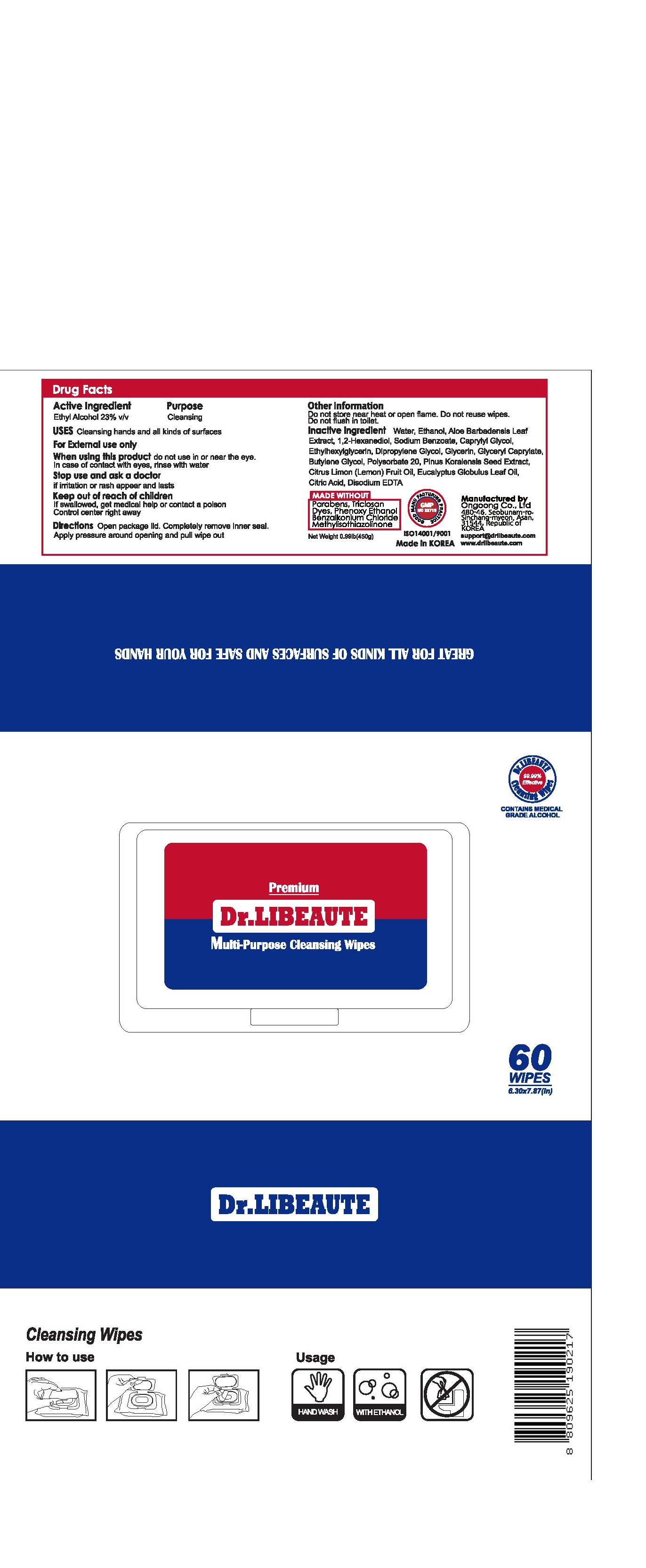 DRUG LABEL: Dr.LIBEAUTE Multi-Purpose Cleansing Wipes
NDC: 74084-0010 | Form: LIQUID
Manufacturer: Ongoong Co Ltd
Category: otc | Type: HUMAN OTC DRUG LABEL
Date: 20200814

ACTIVE INGREDIENTS: ALCOHOL 23 g/100 g
INACTIVE INGREDIENTS: POLYSORBATE 20; GLYCERIN; BUTYLENE GLYCOL; WATER; SODIUM BENZOATE; CAPRYLYL GLYCOL

Drug Facts

ACTIVE INGREDIENT

ethyl alcohol

INACTIVE INGREDIENT

Water,Sodium Benzoate,Polysorbate 20,Caprylyl Glycol,Ethylhexylglycerin,Dipropylene Glycol,Glycerin,Glyceryl Caprylate,Citric Acid,Disodium EDTA,Camellia Sinensis Leaf Extract,Butylene Glycol,Aloe Barbadensis Leaf Extract,fragrance.

PURPOSE

cleansing hands and all kinds of surfaces

KEEP OUT OF REACH OF THE CHILDREN

INDICATIONS AND USAGE

open package lid, completely remove inner seal, apply pressure around opening and pull wipe out

WARNINGS

For external use only.

Flammable, keep away from fire or flame.

When using this product keep out of eyes. If contact with eyes occurs, rinse promptly and thoroughly with water.

Stop use and ask a doctor if significant irritation or sensitization develops.

Keep out of reach of children. If swallowed, get medical help or contact a Poison Control Center right away.

DOSAGE AND ADMINISTRATION

for external use only